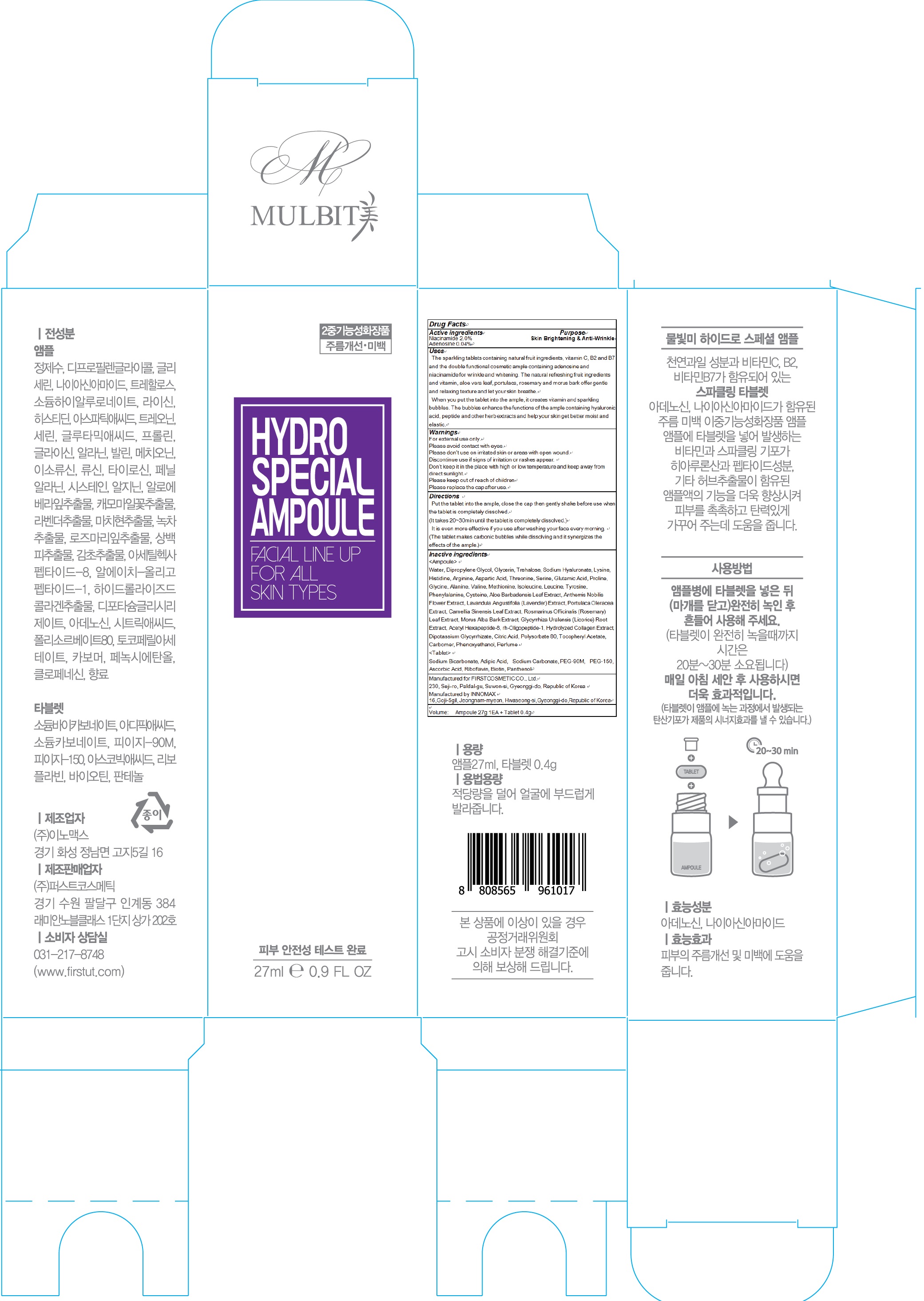 DRUG LABEL: MULBIT Hydro Special Ample
NDC: 71635-080 | Form: LIQUID
Manufacturer: First Cosmetic Co., Ltd
Category: otc | Type: HUMAN OTC DRUG LABEL
Date: 20171020

ACTIVE INGREDIENTS: Niacinamide 0.54 g/27 mL; Adenosine 0.01 g/27 mL
INACTIVE INGREDIENTS: Water; Dipropylene Glycol

ACTIVE INGREDIENT

Active ingredients: Niacinamide 2.0%, Adenosine 0.04%

INACTIVE INGREDIENT

Inactive ingredients:

<Ampoule> Water, Dipropylene Glycol, Glycerin, Trehalose, Sodium Hyaluronate, Lysine, Histidine, Arginine, Aspartic Acid, Threonine, Serine, Glutamic Acid, Proline, Glycine, Alanine, Valine, Methionine, Isoleucine, Leucine, Tyrosine, Phenylalanine, Cysteine, Aloe Barbadensis Leaf Extract, Anthemis Nobilis Flower Extract, Lavandula Angustifolia (Lavender) Extract, Portulaca Oleracea Extract, Camellia Sinensis Leaf Extract, Rosmarinus Officinalis (Rosemary) Leaf Extract, Morus Alba Bark Extract, Glycyrrhiza Uralensis (Licorice) Root Extract, Acetyl Hexapeptide-8, rh-Oligopeptide-1, Hydrolyzed Collagen Extract, Dipotassium Glycyrrhizate, Citric Acid, Polysorbate 80, Tocopheryl Acetate, Carbomer, Phenoxyethanol, Perfume

<Tablet> Sodium Bicarbonate, Adipic Acid, Sodium Carbonate, PEG-90M, PEG-150, Ascorbic Acid, Riboflavin, Biotin, Panthenol

PURPOSE

Purpose: Skin Brightening & Anti wrinkle

WARNINGS

Warnings: For external use only. Please avoid contact with eyes. Please don’t use on irritated skin or areas with open wound. Discontinue use if signs of irritation or rashes appear. Don’t keep it in the place with high or low temperature and keep away from direct sunlight. Please keep out of reach of children Please replace the cap after use.

KEEP OUT OF REACH OF CHILDREN

Uses

Uses: The sparkling tablets containing natural fruit ingredients, vitamin C, B2 and B7 and the double functional cosmetic ample containing adenosine and niacinamide for wrinkle and whitening. The natural refreshing fruit ingredients and vitamin, aloe vera leaf, portulaca, rosemary and morus bark offer gentle and relaxing texture and let your skin breathe. When you put the tablet into the ample, it creates vitamin and sparkling bubbles. The bubbles enhance the functions of the ample containing hyaluronic acid, peptide and other herb extracts and help your skin get better moist and elastic.

Directions

Directions: Put the tablet into the ample, close the cap then gently shake before use when the tablet is completely dissolved. (It takes 20~30min until the tablet is completely dissolved.) It is even more effective if you use after washing your face every morning. (The tablet makes carbonic bubbles while dissolving and it synergizes the effects of the ample.)